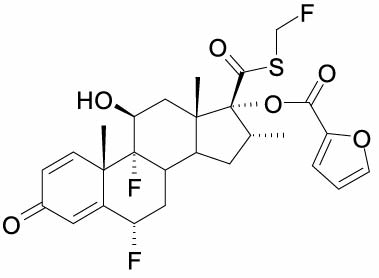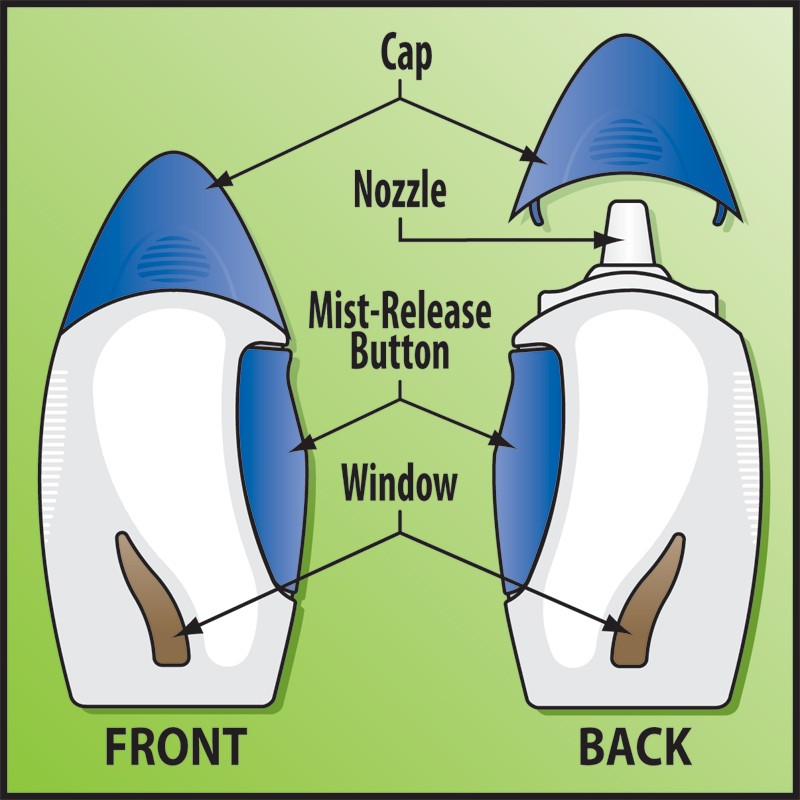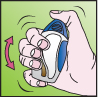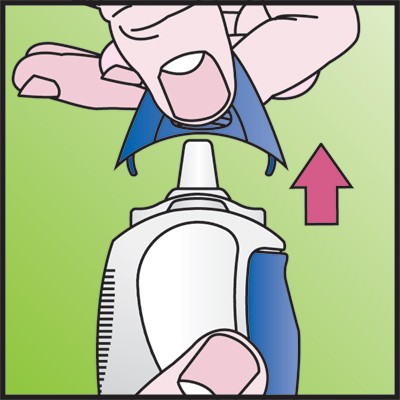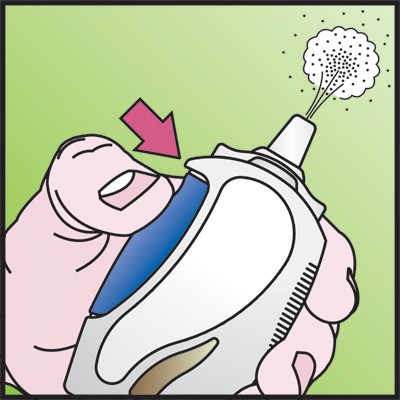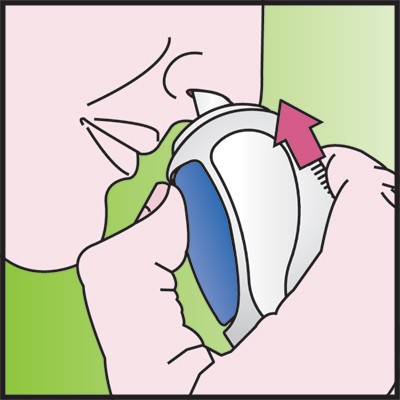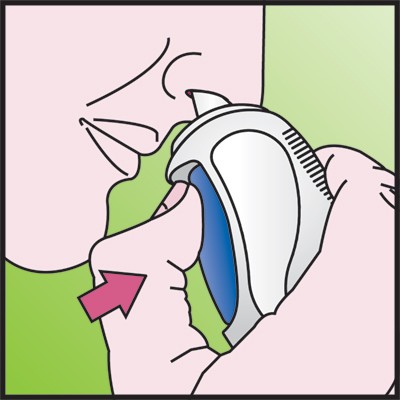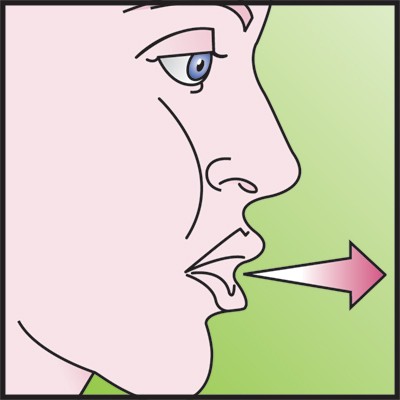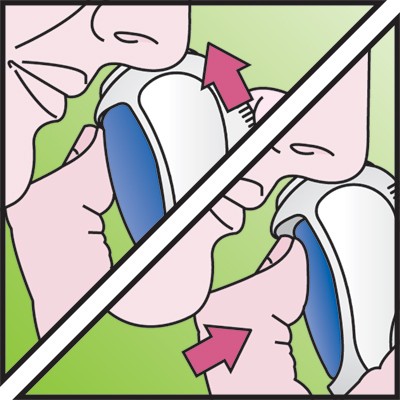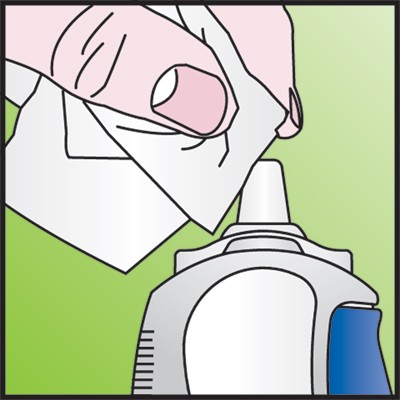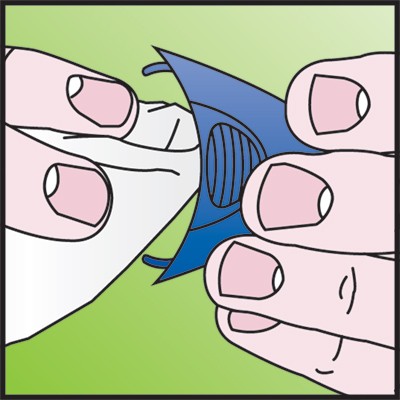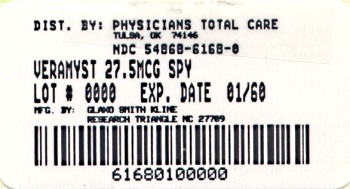 DRUG LABEL: Veramyst
NDC: 54868-6168 | Form: SPRAY, METERED
Manufacturer: Physicians Total Care, Inc.
Category: prescription | Type: HUMAN PRESCRIPTION DRUG LABEL
Date: 20100401

ACTIVE INGREDIENTS: FLUTICASONE FUROATE 27.5 ug/1 1
INACTIVE INGREDIENTS: BENZALKONIUM CHLORIDE; ANHYDROUS DEXTROSE; EDETATE DISODIUM; CELLULOSE, MICROCRYSTALLINE; CARBOXYMETHYLCELLULOSE SODIUM; POLYSORBATE 80; WATER

HIGHLIGHTS OF PRESCRIBING INFORMATION

These highlights do not include all the information needed to use VERAMYST safely and effectively. See full prescribing information for VERAMYST.
VERAMYST (fluticasone furoate) Nasal Spray
Initial U.S. Approval: 2007

RECENT MAJOR CHANGES

Contraindications (4) September 2009

Warnings and Precautions (5.3) September 2009

1 INDICATIONS AND USAGE

VERAMYST Nasal Spray is a corticosteroid indicated for treatment of symptoms of seasonal and perennial allergic rhinitis in adults and children ≥2 years. (1.1)

2 DOSAGE AND ADMINISTRATION

For intranasal use only. Usual starting dosages:

- Adults and adolescents ≥12 years: 110 mcg (2 sprays per nostril) once daily. (2.1)
- Children 2-11 years: 55 mcg (1 spray per nostril) once daily. (2.2)
- Priming information: Prime VERAMYST Nasal Spray before using for the first time, when not used for more than 30 days, or if the cap has been left off the bottle for 5 days or longer. (2)

3 DOSAGE FORMS AND STRENGTHS

Nasal spray: 27.5 mcg of fluticasone furoate in each 50-microliter spray. (3)

Supplied in 10-g bottle containing 120 sprays. (16)

4 CONTRAINDICATIONS

Hypersensitivity to ingredients. (4)

5 WARNINGS AND PRECAUTIONS

- Epistaxis, nasal ulceration, Candida albicans infection, nasal septal perforation, impaired wound healing. Monitor patients periodically for signs of adverse effects on the nasal mucosa. Avoid use in patients with recent nasal ulcers, nasal surgery, or nasal trauma. (5.1)
- Development of glaucoma or posterior subcapsular cataracts. Monitor patients closely with a change in vision or with a history of increased intraocular pressure, glaucoma, and/or cataracts. (5.2)
- Hypersensitivity reactions, including anaphylaxis, angioedema, rash, and urticaria, may occur after administration of VERAMYST Nasal Spray. (5.3)
- Potential worsening of existing tuberculosis; fungal, bacterial, viral, or parasitic infections; or ocular herpes simplex. More serious or even fatal course of chickenpox or measles in susceptible patients. Use caution in patients with the above because of the potential for worsening of these infections. (5.4)
- Hypercorticism and adrenal suppression with very high dosages or at the regular dosage in susceptible individuals. If such changes occur, discontinue VERAMYST Nasal Spray slowly. (5.5)
- Potential reduction in growth velocity in children. Monitor growth routinely in pediatric patients receiving VERAMYST Nasal Spray. (5.7, 8.4)

6 ADVERSE REACTIONS

The most common adverse reactions (>1% incidence) included headache, epistaxis, pharyngolaryngeal pain, nasal ulceration, back pain, pyrexia, and cough. (6.1)

To report SUSPECTED ADVERSE REACTIONS, contact GlaxoSmithKline at 1-888-825-5249 or FDA at 1-800-FDA-1088 or www.fda.gov/medwatch.

7 DRUG INTERACTIONS

Potent inhibitors of cytochrome P450 (CYP) 3A4 may increase exposure to fluticasone furoate.

- Coadministration of ritonavir is not recommended. (5.5, 7)
- Use caution with coadministration of other potent CYP 3A4 inhibitors, such as ketoconazole. (5.6, 7)

8 USE IN SPECIFIC POPULATIONS

Hepatic impairment may increase exposure to fluticasone furoate. Use with caution in patients with severe hepatic impairment. (8.6)

FULL PRESCRIBING INFORMATION

1 INDICATIONS AND USAGE

1.1 Treatment of Allergic Rhinitis

VERAMYST® (fluticasone furoate) Nasal Spray is indicated for the treatment of the symptoms of seasonal and perennial allergic rhinitis in patients aged 2 years and older.

2 DOSAGE AND ADMINISTRATION

Administer VERAMYST Nasal Spray by the intranasal route only. Prime VERAMYST Nasal Spray before using for the first time by shaking the contents well and releasing 6 sprays into the air away from the face. When VERAMYST Nasal Spray has not been used for more than 30 days or if the cap has been left off the bottle for 5 days or longer, prime the pump again until a fine mist appears. Shake VERAMYST Nasal Spray well before each use.

2.1 Adults and Adolescents Aged 12 Years and Older

The recommended starting dosage is 110 mcg once daily administered as 2 sprays (27.5 mcg/spray) in each nostril. Titrate an individual patient to the minimum effective dosage to reduce the possibility of side effects. When the maximum benefit has been achieved and symptoms have been controlled, reducing the dosage to 55 mcg (1 spray in each nostril) once daily may be effective in maintaining control of allergic rhinitis symptoms.

2.2 Children Aged 2 to 11 Years

The recommended starting dosage in children is 55 mcg once daily administered as 1 spray (27.5 mcg/spray) in each nostril. Children not adequately responding to 55 mcg may use 110 mcg (2 sprays in each nostril) once daily. Once symptoms have been controlled, the dosage may be decreased to 55 mcg once daily.

3 DOSAGE FORMS AND STRENGTHS

VERAMYST Nasal Spray is a nasal spray suspension. Each spray (50 microliters) delivers 27.5 mcg of fluticasone furoate.

4 CONTRAINDICATIONS

VERAMYST Nasal Spray is contraindicated in patients with hypersensitivity to any of its ingredients [see Warnings and Precautions (5.3)].

5 WARNINGS AND PRECAUTIONS

5.1 Local Nasal Effects

Epistaxis and Nasal Ulceration

In clinical studies of 2 to 52 weeks’ duration, epistaxis and nasal ulcerations were observed more frequently and some epistaxis events were more severe in patients treated with VERAMYST Nasal Spray than those who received placebo [see Adverse Reactions (6)].

Candida Infection

Evidence of localized infections of the nose with Candida albicans was seen on nasal exams in 7 of 2,745 patients treated with VERAMYST Nasal Spray during clinical trials and was reported as an adverse event in 3 patients. When such an infection develops, it may require treatment with appropriate local therapy and discontinuation of VERAMYST Nasal Spray. Therefore, patients using VERAMYST Nasal Spray over several months or longer should be examined periodically for evidence of Candida infection or other signs of adverse effects on the nasal mucosa.

Nasal Septal Perforation

Instances of nasal septal perforation have been reported in patients following the intranasal application of corticosteroids. There were no instances of nasal septal perforation observed in clinical studies with VERAMYST Nasal Spray.

Impaired Wound Healing

Because of the inhibitory effect of corticosteroids on wound healing, patients who have experienced recent nasal ulcers, nasal surgery, or nasal trauma should not use VERAMYST Nasal Spray until healing has occurred.

5.2 Glaucoma and Cataracts

Nasal and inhaled corticosteroids may result in the development of glaucoma and/or cataracts. Therefore, close monitoring is warranted in patients with a change in vision or with a history of increased intraocular pressure, glaucoma, and/or cataracts.

Glaucoma and cataract formation was evaluated with intraocular pressure measurements and slit lamp examinations in 1 controlled 12-month study in 806 adolescent and adult patients aged 12 years and older and in 1 controlled 12-week study in 558 children aged 2 to 11 years. The patients had perennial allergic rhinitis and were treated with either VERAMYST Nasal Spray (110 mcg once daily in adult and adolescent patients and 55 or 110 mcg once daily in pediatric patients) or placebo. Intraocular pressure remained within the normal range (<21 mmHg) in ≥98% of the patients in any treatment group in both studies. However, in the 12-month study in adolescents and adults, 12 patients, all treated with VERAMYST Nasal Spray 110 mcg once daily, had intraocular pressure measurements that increased above normal levels (≥21 mmHg). In the same study, 7 patients (6 treated with VERAMYST Nasal Spray 110 mcg once daily and 1 patient treated with placebo) had cataracts identified during the study that were not present at baseline.

5.3 Hypersensitivity Reactions, Including Anaphylaxis

Hypersensitivity reactions, including anaphylaxis, angioedema, rash, and urticaria, may occur after administration of VERAMYST Nasal Spray. Discontinue VERAMYST Nasal Spray if such reactions occur [see Contraindications (4)].

5.4 Immunosuppression

Persons who are using drugs that suppress the immune system are more susceptible to infections than healthy individuals. Chickenpox and measles, for example, can have a more serious or even fatal course in susceptible children or adults using corticosteroids. In children or adults who have not had these diseases or have not been properly immunized, particular care should be taken to avoid exposure. How the dose, route, and duration of corticosteroid administration affect the risk of developing a disseminated infection is not known. The contribution of the underlying disease and/or prior corticosteroid treatment to the risk is also not known. If a patient is exposed to chickenpox, prophylaxis with varicella zoster immune globulin (VZIG) may be indicated. If a patient is exposed to measles, prophylaxis with pooled intramuscular immunoglobulin (IG) may be indicated. (See the respective package inserts for complete VZIG and IG prescribing information.) If chickenpox or measles develops, treatment with antiviral agents may be considered.

Corticosteroids should be used with caution, if at all, in patients with active or quiescent tuberculous infections of the respiratory tract; untreated local or systemic fungal or bacterial infections; systemic viral or parasitic infections; or ocular herpes simplex because of the potential for worsening of these infections.

5.5 Hypothalamic-Pituitary-Adrenal Axis Effects

Hypercorticism and Adrenal Suppression

When intranasal steroids are used at higher than recommended dosages or in susceptible individuals at recommended dosages, systemic corticosteroid effects such as hypercorticism and adrenal suppression may appear. If such changes occur, the dosage of VERAMYST Nasal Spray should be discontinued slowly, consistent with accepted procedures for discontinuing oral corticosteroid therapy.

The replacement of a systemic corticosteroid with a topical corticosteroid can be accompanied by signs of adrenal insufficiency. In addition, some patients may experience symptoms of corticosteroid withdrawal, e.g., joint and/or muscular pain, lassitude, and depression. Patients previously treated for prolonged periods with systemic corticosteroids and transferred to topical corticosteroids should be carefully monitored for acute adrenal insufficiency in response to stress. In those patients who have asthma or other clinical conditions requiring long-term systemic corticosteroid treatment, rapid decreases in systemic corticosteroid dosages may cause a severe exacerbation of their symptoms.

5.6 Use of Cytochrome P450 3A4 Inhibitors

Co-administration with ritonavir is not recommended because of the risk of systemic effects secondary to increased exposure to fluticasone furoate. Use caution with the co-administration of VERAMYST Nasal Spray and other potent cytochrome P450 (CYP) 3A4 inhibitors, such as ketoconazole [see Drug Interactions (7)].

5.7 Effect on Growth

Corticosteroids may cause a reduction in growth velocity when administered to pediatric patients. Monitor the growth routinely of pediatric patients receiving VERAMYST Nasal Spray. To minimize the systemic effects of intranasal corticosteroids, including VERAMYST Nasal Spray, titrate each patient’s dose to the lowest dosage that effectively controls his/her symptoms [see Use in Specific Populations (8.4)].

6 ADVERSE REACTIONS

Systemic and local corticosteroid use may result in the following:

- Epistaxis, ulcerations, Candida albicans infection, impaired wound healing [see Warnings and Precautions (5.1)]
- Cataracts and glaucoma [see Warnings and Precautions (5.2)]
- Immunosuppression [see Warnings and Precautions (5.4)]
- Hypothalamic-pituitary-adrenal (HPA) axis effects, including growth reduction [see Warnings and Precautions (5.5), Use in Specific Populations (8.4)]

6.1 Clinical Trials Experience

The safety data described below reflect exposure to VERAMYST Nasal Spray in 1,563 patients with seasonal or perennial allergic rhinitis in 9 controlled clinical trials of 2 to 12 weeks’ duration. The data from adults and adolescents are based upon 6 clinical trials in which 768 patients with seasonal or perennial allergic rhinitis (473 females and 295 males aged 12 years and older) were treated with VERAMYST Nasal Spray 110 mcg once daily for 2 to 6 weeks. The racial distribution of adult and adolescent patients receiving VERAMYST Nasal Spray was 82% white, 5% black, and 13% other. The data from pediatric patients are based upon 3 clinical trials in which 795 children with seasonal or perennial rhinitis (352 females and 443 males aged 2 to 11 years) were treated with VERAMYST Nasal Spray 55 or 110 mcg once daily for 2 to 12 weeks. The racial distribution of pediatric patients receiving VERAMYST Nasal Spray was 75% white, 11% black, and 14% other.

Because clinical trials are conducted under widely varying conditions, adverse reaction rates observed in the clinical trials of a drug cannot be directly compared with rates in the clinical trials of another drug and may not reflect the rates observed in practice.

Adults and Adolescents Aged 12 Years and Older

Overall adverse reactions were reported with approximately the same frequency by patients treated with VERAMYST Nasal Spray and those receiving placebo. Less than 3% of patients in clinical trials discontinued treatment because of adverse reactions. The rate of withdrawal among patients receiving VERAMYST Nasal Spray was similar or lower than the rate among patients receiving placebo.

Table 1 displays the common adverse reactions (>1% in any patient group receiving VERAMYST Nasal Spray) that occurred more frequently in patients aged 12 years and older treated with VERAMYST Nasal Spray compared with placebo-treated patients.

Table 1. Adverse Reactions With >1% Incidence in Controlled Clinical Trials of 2 to 6 Weeks’ Duration With VERAMYST Nasal Spray in Adult and Adolescent Patients With Seasonal or Perennial Allergic Rhinitis
Adverse Event | Adult and Adolescent Patients; Aged 12 Years and Older
Adverse Event | Vehicle Placebo; (n = 774) | VERAMYST Nasal Spray; 110 mcg Once Daily; (n = 768)
Headache | 54 (7%) | 72 (9%)
Epistaxis | 32 (4%) | 45 (6%)
Pharyngolaryngeal pain | 8 (1%) | 15 (2%)
Nasal ulceration | 3 (<1%) | 11 (1%)
Back pain | 7 (<1%) | 9 (1%)

There were no differences in the incidence of adverse reactions based on gender or race. Clinical trials did not include sufficient numbers of patients aged 65 years and older to determine whether they respond differently from younger subjects.

Pediatric Patients Aged 2 to 11 Years

In the 3 clinical trials in pediatric patients aged 2 to <12 years, overall adverse reactions were reported with approximately the same frequency by patients treated with VERAMYST Nasal Spray and those receiving placebo. Table 2 displays the common adverse reactions (>3% in any patient group receiving VERAMYST Nasal Spray), that occurred more frequently in patients aged 2 to 11 years treated with VERAMYST Nasal Spray compared with placebo-treated patients.

Table 2. Adverse Reactions With >3% Incidence in Controlled Clinical Trials of 2 to 12 Weeks’ Duration With VERAMYST Nasal Spray in Pediatric Patients With Seasonal or Perennial Allergic Rhinitis
Adverse Event | Pediatric Patients Aged 2 to <12 Years
Adverse Event | Vehicle Placebo; (n = 429) | VERAMYST Nasal Spray; 55 mcg Once Daily; (n = 369) | VERAMYST Nasal Spray; 110 mcg Once Daily; (n = 426)
Headache | 31 (7%) | 28 (8%) | 33 (8%)
Nasopharyngitis | 21 (5%) | 20 (5%) | 21 (5%)
Epistaxis | 19 (4%) | 17 (5%) | 17 (4%)
Pyrexia | 7 (2%) | 17 (5%) | 19 (4%)
Pharyngolaryngeal pain | 14 (3%) | 16 (4%) | 12 (3%)
Cough | 12 (3%) | 12 (3%) | 16 (4%)

There were no differences in the incidence of adverse reactions based on gender or race. Pyrexia occurred more frequently in children aged 2 to <6 years compared with children aged 6 to <12 years.

Long-Term (52-Week) Safety Trial

In a 52-week, placebo-controlled, long-term safety trial, 605 patients (307 females and 298 males aged 12 years and older) with perennial allergic rhinitis were treated with VERAMYST Nasal Spray 110 mcg once daily for 12 months and 201 were treated with placebo nasal spray. While most adverse reactions were similar in type and rate between the treatment groups, epistaxis occurred more frequently in patients who received VERAMYST Nasal Spray (123/605, 20%) than in patients who received placebo (17/201, 8%). Epistaxis tended to be more severe in patients treated with VERAMYST Nasal Spray. All 17 reports of epistaxis that occurred in patients who received placebo were of mild intensity, while 83, 39, and 1 of the total 123 epistaxis events in patients treated with VERAMYST Nasal Spray were of mild, moderate, and severe intensity, respectively. No patient experienced a nasal septal perforation during this trial.

6.2 Postmarketing Experience

In addition to adverse reactions reported from clinical trials, the following adverse reactions have been identified during postmarketing use of VERAMYST Nasal Spray. Because these reactions are reported voluntarily from a population of uncertain size, it is not always possible to reliably estimate their frequency or establish a causal relationship to drug exposure. These events have been chosen for inclusion due to either their seriousness, frequency of reporting, or causal connection to fluticasone furoate or a combination of these factors.

Immune System Disorders: Hypersensitivity reactions, including anaphylaxis, angioedema, rash, and urticaria.

7 DRUG INTERACTIONS

Fluticasone furoate is cleared by extensive first-pass metabolism mediated by CYP3A4. In a drug interaction study of intranasal fluticasone furoate and the CYP3A4 inhibitor ketoconazole given as a 200-mg once-daily dose for 7 days, 6 of 20 subjects receiving fluticasone furoate and ketoconazole had measurable but low levels of fluticasone furoate compared with 1 of 20 receiving fluticasone furoate and placebo. Based on this study and the low systemic exposure, there was a 5% reduction in 24-hour serum cortisol levels with ketoconazole compared with placebo. The data from this study should be carefully interpreted because the study was conducted with ketoconazole 200 mg once daily rather than 400 mg, which is the maximum recommended dosage. Therefore, caution is required with the co-administration of VERAMYST Nasal Spray and ketoconazole or other potent CYP3A4 inhibitors.

Based on data with another glucocorticoid, fluticasone propionate, metabolized by CYP3A4, co-administration of VERAMYST Nasal Spray with the potent CYP3A4 inhibitor ritonavir is not recommended because of the risk of systemic effects secondary to increased exposure to fluticasone furoate. High exposure to corticosteroids increases the potential for systemic side effects, such as cortisol suppression.

Enzyme induction and inhibition data suggest that fluticasone furoate is unlikely to significantly alter the cytochrome P450-mediated metabolism of other compounds at clinically relevant intranasal dosages.

8 USE IN SPECIFIC POPULATIONS

8.1 Pregnancy

Teratogenic Effects

Pregnancy Category C. Corticosteroids have been shown to be teratogenic in laboratory animals when administered systemically at relatively low dosage levels.

There were no teratogenic effects in rats and rabbits at inhaled fluticasone furoate dosages of up to 91 and 8 mcg/kg/day, respectively (approximately 7 and 1 times, respectively, the maximum recommended daily intranasal dose in adults on a mcg/m^2 basis). There was also no effect on pre- or post-natal development in rats treated with up to 27 mcg/kg/day by inhalation during gestation and lactation (approximately 2 times the maximum recommended daily intranasal dose in adults on a mcg/m^2 basis).

There are no adequate and well-controlled studies in pregnant women. VERAMYST Nasal Spray should be used during pregnancy only if the potential benefit justifies the potential risk to the fetus.

Nonteratogenic Effects

Hypoadrenalism may occur in infants born of mothers receiving corticosteroids during pregnancy. Such infants should be carefully monitored.

8.3 Nursing Mothers

It is not known whether fluticasone furoate is excreted in human breast milk. However, other corticosteroids have been detected in human milk. Since there are no data from controlled trials on the use of intranasal fluticasone furoate by nursing mothers, caution should be exercised when VERAMYST Nasal Spray is administered to a nursing woman.

8.4 Pediatric Use

Controlled clinical trials with VERAMYST Nasal Spray included 1,224 patients aged 2 to 11 years and 344 adolescent patients aged 12 to 17 years [see Clinical Studies (14)]. The safety and effectiveness of VERAMYST Nasal Spray in children younger than 2 years have not been established.

Controlled clinical studies have shown that intranasal corticosteroids may cause a reduction in growth velocity in pediatric patients. This effect has been observed in the absence of laboratory evidence of HPA axis suppression, suggesting that growth velocity is a more sensitive indicator of systemic corticosteroid exposure in pediatric patients than some commonly used tests of HPA axis function. The long-term effects of reduction in growth velocity associated with intranasal corticosteroids, including the impact on final adult height, are unknown. The potential for “catch-up” growth following discontinuation of treatment with intranasal corticosteroids has not been adequately studied. The growth of pediatric patients receiving intranasal corticosteroids, including VERAMYST Nasal Spray, should be monitored routinely (e.g., via stadiometry). The potential growth effects of prolonged treatment should be weighed against the clinical benefits obtained and the risks/benefits of treatment alternatives. To minimize the systemic effects of intranasal corticosteroids, including VERAMYST Nasal Spray, each patient’s dose should be titrated to the lowest dosage that effectively controls his/her symptoms.

The potential for VERAMYST Nasal Spray to cause growth suppression in susceptible patients or when given at higher than recommended dosages cannot be ruled out.

8.5 Geriatric Use

Clinical studies of VERAMYST Nasal Spray did not include sufficient numbers of subjects aged 65 years and older to determine whether they respond differently from younger subjects. Other reported clinical experience has not identified differences in responses between the elderly and younger patients. In general, dose selection for an elderly patient should be cautious, usually starting at the low end of the dosing range, reflecting the greater frequency of decreased hepatic, renal, or cardiac function, and of concomitant disease or other drug therapy.

8.6 Hepatic Impairment

Use VERAMYST Nasal Spray with caution in patients with severe hepatic impairment [see Clinical Pharmacology (12.3)].

8.7 Renal Impairment

No dosage adjustment is required in patients with renal impairment [see Clinical Pharmacology (12.3)].

10 OVERDOSAGE

Chronic overdosage may result in signs/symptoms of hypercorticism [see Warnings and Precautions (5.4)]. There are no data on the effects of acute or chronic overdosage with VERAMYST Nasal Spray. Because of low systemic bioavailability and an absence of acute drug-related systemic findings in clinical studies (with dosages of up to 440 mcg/day for 2 weeks [4 times the maximum recommended daily dose]), overdose is unlikely to require any therapy other than observation.

Intranasal administration of up to 2,640 mcg/day (24 times the recommended adult dose) of fluticasone furoate was administered to healthy human volunteers for 3 days. Single- and repeat-dose studies with orally inhaled fluticasone furoate doses of 50 to 4,000 mcg have shown decreased mean serum cortisol at doses of 500 mcg or higher. The oral median lethal dose in mice and rats was >2,000 mg/kg (approximately 74,000 and 147,000 times, respectively, the maximum recommended daily intranasal dose in adults and 52,000 and 105,000 times, respectively, the maximum recommended daily intranasal dose in children, on a mcg/m^2 basis).

Acute overdosage with the intranasal dosage form is unlikely since 1 bottle of VERAMYST Nasal Spray contains approximately 3 mg of fluticasone furoate, and the bioavailability of fluticasone furoate is <1% for 2.64 mg/day given intranasally and 1% for 2 mg/day given as an oral solution.

11 DESCRIPTION

Fluticasone furoate, the active component of VERAMYST Nasal Spray, is a synthetic fluorinated corticosteroid having the chemical name (6α,11β,16α,17α)-6,9-difluoro-17-{[(fluoro-methyl)thio]carbonyl}-11-hydroxy-16-methyl-3-oxoandrosta-1,4-dien-17-yl 2-furancarboxylate and the following chemical structure:

Fluticasone furoate is a white powder with a molecular weight of 538.6, and the empirical formula is C27H29F3O6S. It is practically insoluble in water.

VERAMYST Nasal Spray is an aqueous suspension of micronized fluticasone furoate for topical administration to the nasal mucosa by means of a metering (50 microliters), atomizing spray pump. After initial priming [see Dosage and Administration (2)], each actuation delivers 27.5 mcg of fluticasone furoate in a volume of 50 microliters of nasal spray suspension. VERAMYST Nasal Spray also contains 0.015% w/w benzalkonium chloride, dextrose anhydrous, edetate disodium, microcrystalline cellulose and carboxymethylcellulose sodium, polysorbate 80, and purified water. It has a pH of approximately 6.

12 CLINICAL PHARMACOLOGY

12.1 Mechanism of Action

Fluticasone furoate is a synthetic trifluorinated corticosteroid with potent anti-inflammatory activity. The precise mechanism through which fluticasone furoate affects rhinitis symptoms is not known. Corticosteroids have been shown to have a wide range of actions on multiple cell types (e.g., mast cells, eosinophils, neutrophils, macrophages, lymphocytes) and mediators (e.g., histamine, eicosanoids, leukotrienes, cytokines) involved in inflammation. Specific effects of fluticasone furoate demonstrated in in vitro and in vivo models included activation of the glucocorticoid response element, inhibition of pro-inflammatory transcription factors such as NFkB, and inhibition of antigen-induced lung eosinophilia in sensitized rats.

Fluticasone furoate has been shown in vitro to exhibit a binding affinity for the human glucocorticoid receptor that is approximately 29.9 times that of dexamethasone and 1.7 times that of fluticasone propionate. The clinical relevance of these findings is unknown.

12.2 Pharmacodynamics

Adrenal Function

The effects of VERAMYST Nasal Spray on adrenal function have been evaluated in 4 controlled clinical trials in patients with perennial allergic rhinitis. Two 6-week clinical trials were designed specifically to assess the effect of VERAMYST Nasal Spray on the HPA axis with assessments of both 24-hour urinary cortisol excretion and serum cortisol levels in domiciled patients. In addition, one 52-week safety study and one 12-week safety and efficacy study included assessments of 24-hour urinary cortisol excretion. Details of the studies and results are described below. In all 4 studies, since serum fluticasone determinations were generally below the limit of quantification, compliance was assured by efficacy assessments.

Clinical Trials Specifically Designed to Assess Hypothalamic-Pituitary-Adrenal Axis Effect

In a 6-week randomized, double-blind, parallel-group study in adult and adolescent patients aged 12 years and older with perennial allergic rhinitis, VERAMYST Nasal Spray 110 mcg was compared with both placebo nasal spray and prednisone as a positive-control group that received prednisone 10 mg orally once daily for the final 7 days of the treatment period. Adrenal function was assessed by 24-hour urinary cortisol excretion before and after 6 weeks of treatment and by serial serum cortisol levels. Patients were domiciled for collection of 24-hour urinary cortisol. After 6 weeks of treatment, there was a change from baseline in the mean 24-hour urinary cortisol excretion in the group treated with VERAMYST Nasal Spray (n = 43) of -1.16 mcg/day compared with -3.48 mcg/day in the placebo group (n = 42). The difference from placebo in the group treated with VERAMYST Nasal Spray was 2.32 mcg/day (95% CI: -6.76, 11.39). Urinary cortisol data were not available for the positive-control (prednisone) treatment group. For serum cortisol levels, after 6 weeks of treatment there was a change from baseline in the mean (0-24 hours) of -0.38 and 0.08 mcg/dL for the group treated with VERAMYST Nasal Spray (n = 43) and the placebo group (n = 44), respectively, with a difference between the group treated with VERAMYST Nasal Spray and the placebo group of -0.47 mcg/dL (95% CI: -1.31, 0.37). For comparison, in the positive-control (prednisone, n = 12) treatment group, there was a change in mean serum cortisol (0-24 hours) from baseline of -4.49 mcg/dL with a difference between the prednisone and placebo group of -4.57 mcg/dL (95% CI: -5.83, -3.31).

The second 6-week study conducted in children aged 2 to 11 years was of similar design to the adult study, including adrenal function assessments, but did not include a prednisone positive-control arm. Patients were treated once daily with VERAMYST Nasal Spray 110 mcg or placebo nasal spray. After 6 weeks of treatment, there was a change in the mean 24-hour urinary cortisol excretion in the group treated with VERAMYST Nasal Spray (n = 43) of 0.49 mcg/day compared with 1.92 mcg/day in the placebo group (n = 41), with a difference between the group treated with VERAMYST Nasal Spray and the placebo group of -1.43 mcg/day (95% CI: -5.21, 2.35). For serum cortisol levels, after 6 weeks, there was a change from baseline in mean (0-24 hours) of -0.34 and -0.23 mcg/dL for the group treated with VERAMYST Nasal Spray (n = 48) and for the placebo group (n = 47), respectively, with a difference between the group treated with VERAMYST Nasal Spray and the placebo group of -0.11 mcg/dL (95% CI: -0.88, 0.66).

Additional Hypothalamic-Pituitary-Adrenal Axis Assessments

In the 52-week safety trial in adolescents and adults aged 12 years and older with perennial allergic rhinitis, VERAMYST Nasal Spray 110 mcg (n = 605) was compared with placebo nasal spray (n = 201). Adrenal function was assessed by 24-hour urinary cortisol excretion in a subset of patients who received VERAMYST Nasal Spray (n = 370) or placebo (n = 120) before and after 52 weeks of treatment. After 52 weeks of treatment, the mean change from baseline 24-hour urinary cortisol excretion was 5.84 mcg/day in the group treated with VERAMYST Nasal Spray and 3.34 mcg/day in the placebo group. The difference from placebo in mean change from baseline 24-hour urinary cortisol excretion was 2.50 mcg/day (95% CI: -5.49, 10.49).

In the 12-week safety and efficacy trial in children aged 2 to 11 years with perennial allergic rhinitis, VERAMYST Nasal Spray 55 mcg (n = 185) and VERAMYST Nasal Spray 110 mcg (n = 185) were compared with placebo nasal spray (n = 188). Adrenal function was assessed by measurement of 24-hour urinary free cortisol in a subset of patients who were aged 6 to 11 years (103 to 109 patients per group) before and after 12 weeks of treatment. After 12 weeks of treatment, there was a decrease in mean 24-hour urinary cortisol excretion from baseline in the group treated with VERAMYST Nasal Spray 55 mcg (n = 109) of -2.93 mcg/day and in the group treated with VERAMYST Nasal Spray 110 mcg (n = 103) of -2.07 mcg/day compared with an increase in the placebo group (n = 107) of 0.08 mcg/day. The difference from placebo in mean change from baseline in 24-hour urinary cortisol excretion for the group treated with VERAMYST Nasal Spray 55 mcg was -3.01 mcg/day (95% CI: -6.16, 0.13) and -2.14 mcg/day (95% CI: -5.33, 1.04) for the group treated with VERAMYST Nasal Spray 110 mcg.

When the results of the HPA axis assessments described above are taken as a whole, an effect of intranasal fluticasone furoate on adrenal function cannot be ruled out, especially in pediatric patients.

Cardiac Effects

A QT/QTc study did not demonstrate an effect of fluticasone furoate administration on the QTc interval. The effect of a single dose of 4,000 mcg of orally inhaled fluticasone furoate on the QTc interval was evaluated over 24 hours in 40 healthy male and female subjects in a placebo and positive (a single dose of 400 mg oral moxifloxacin) controlled cross-over study. The QTcF maximal mean change from baseline following fluticasone furoate was similar to that observed with placebo with a treatment difference of 0.788 msec (90% CI: -1.802, 3.378). In contrast, moxifloxacin given as a 400-mg tablet resulted in prolongation of the QTcF maximal mean change from baseline compared with placebo with a treatment difference of 9.929 msec (90% CI: 7.339, 12.520). While a single dose of fluticasone furoate had no effect on the QTc interval, the effects of fluticasone furoate may not be at steady state following single dose. The effect of fluticasone furoate on the QTc interval following multiple dose administration is unknown.

12.3 Pharmacokinetics

Absorption

Following intranasal administration of fluticasone furoate, most of the dose is eventually swallowed and undergoes incomplete absorption and extensive first-pass metabolism in the liver and gut, resulting in negligible systemic exposure. At the highest recommended intranasal dosage of 110 mcg once daily for up to 12 months in adults and up to 12 weeks in children, plasma concentrations of fluticasone furoate are typically not quantifiable despite the use of a sensitive HPLC-MS/MS assay with a lower limit of quantification (LOQ) of 10 pg/mL. However, in a few isolated cases (<0.3%) fluticasone furoate was detected in high concentrations above 500 pg/mL, and in a single case the concentration was as high as 1,430 pg/mL in the 52-week study. There was no relationship between these concentrations and cortisol levels in these subjects. The reasons for these high concentrations are unknown.

Absolute bioavailability was evaluated in 16 male and female subjects following supratherapeutic dosages of fluticasone furoate (880 mcg given intranasally at 8-hour intervals for 10 doses, or 2,640 mcg/day). The average absolute bioavailability was 0.50% (90% CI: 0.34%, 0.74%).

Due to the low bioavailability by the intranasal route, the majority of the pharmacokinetic data was obtained via other routes of administration. Studies using oral solution and intravenous dosing of radiolabeled drug have demonstrated that at least 30% of fluticasone furoate is absorbed and then rapidly cleared from plasma. Oral bioavailability is on average 1.26%, and the majority of the circulating radioactivity is due to inactive metabolites.

Distribution

Following intravenous administration, the mean volume of distribution at steady state is 608 L.

Binding of fluticasone furoate to human plasma proteins is greater than 99%.

Metabolism

In vivo studies have revealed no evidence of cleavage of the furoate moiety to form fluticasone. Fluticasone furoate is cleared (total plasma clearance of 58.7 L/h) from systemic circulation principally by hepatic metabolism via CYP3A4. The principal route of metabolism is hydrolysis of the S-fluoromethyl carbothioate function to form the inactive 17β-carboxylic acid metabolite.

Elimination

Fluticasone furoate and its metabolites are eliminated primarily in the feces, accounting for approximately 101% and 90% of the orally and intravenously administered dose, respectively. Urinary excretion accounted for approximately 1% and 2% of the orally and intravenously administered dose, respectively. The elimination phase half-life averaged 15.1 hours following intravenous administration.

Population Pharmacokinetics

Fluticasone furoate is typically not quantifiable in plasma following intranasal dosing of 110 mcg once daily with the exception of isolated cases of very high plasma levels (see Absorption). Overall, quantifiable levels (>10 pg/mL) were observed in <31% of patients aged 12 years and older and in <16% of children (aged 2 to 11 years) following intranasal dosing of 110 mcg once daily and in <7% of children following intranasal dosing of 55 mcg once daily. There was no evidence to suggest that the presence or absence of detectable levels of fluticasone furoate was related to gender, age, or race.

Hepatic Impairment

Reduced liver function may affect the elimination of corticosteroids. Since fluticasone furoate undergoes extensive first-pass metabolism by the hepatic CYP3A4, the pharmacokinetics of fluticasone furoate may be altered in patients with hepatic impairment. A study of a single 400-mcg dose of orally inhaled fluticasone furoate in patients with moderate hepatic impairment (Child-Pugh Class B) resulted in increased Cmax (42%) and AUC(0-∞) (172%), resulting in an approximately 20% reduction in serum cortisol level in patients with hepatic impairment compared with healthy subjects. The systemic exposure would be expected to be higher than that observed had the study been conducted after multiple doses and/or in patients with severe hepatic impairment. Therefore, use VERAMYST Nasal Spray with caution in patients with severe hepatic impairment.

Renal Impairment

Fluticasone furoate is not detectable in urine from healthy subjects following intranasal dosing. Less than 1% of dose-related material is excreted in urine. No dosage adjustment is required in patients with renal impairment.

13 NONCLINICAL TOXICOLOGY

13.1 Carcinogenesis, Mutagenesis, Impairment of Fertility

Fluticasone furoate produced no treatment-related increases in the incidence of tumors in 2-year inhalation studies in rats and mice at doses of up to 9 and 19 mcg/kg/day, respectively (less than the maximum recommended daily intranasal dose in adults and children on a mcg/m^2 basis).

Fluticasone furoate did not induce gene mutation in bacteria or chromosomal damage in a mammalian cell mutation test in mouse lymphoma L5178Y cells in vitro. There was also no evidence of genotoxicity in the in vivo micronucleus test in rats.

No evidence of impairment of fertility was observed in reproductive studies conducted in male and female rats at inhaled fluticasone furoate doses of up to 24 and 91 mcg/kg/day, respectively (approximately 2 and 7 times, respectively, the maximum recommended daily intranasal dose in adults on a mcg/m^2 basis).

14 CLINICAL STUDIES

14.1 Seasonal and Perennial Allergic Rhinitis

Adult and Adolescent Patients Aged 12 Years and Older

The efficacy and safety of VERAMYST Nasal Spray was evaluated in 5 randomized, double-blind, parallel-group, multicenter, placebo-controlled clinical trials of 2 to 4 weeks’ duration in adult and adolescent patients aged 12 years and older with symptoms of seasonal or perennial allergic rhinitis. The 5 clinical trials included one 2-week dose-ranging trial in patients with seasonal allergic rhinitis, three 2-week confirmatory efficacy trials in patients with seasonal allergic rhinitis, and one 4-week efficacy trial in patients with perennial allergic rhinitis. These trials included 1,829 patients (697 males and 1,132 females). About 75% of patients were Caucasian, and the mean age was 36 years. Of these patients, 722 received VERAMYST Nasal Spray 110 mcg once daily administered as 2 sprays in each nostril.

Assessment of efficacy was based on total nasal symptom score (TNSS). TNSS is calculated as the sum of the patients’ scoring of the 4 individual nasal symptoms (rhinorrhea, nasal congestion, sneezing, and nasal itching) on a 0 to 3 categorical severity scale (0 = absent, 1 = mild, 2 = moderate, 3 = severe) as reflective(rTNSS) or instantaneous (iTNSS). rTNSS required the patients to record symptom severity over the previous 12 hours; iTNSS required patients to record symptom severity at the time immediately prior to the next dose. Morning and evening rTNSS scores were averaged over the treatment period and the difference from placebo in the change from baseline rTNSS was the primary efficacy endpoint. The morning iTNSS (AM iTNSS) reflects the TNSS at the end of the 24-hour dosing interval and is an indication of whether the effect was maintained over the 24-hour dosing interval.

Additional secondary efficacy variables were assessed, including the total ocular symptom score (TOSS) and the Rhinoconjunctivitis Quality of Life Questionnaire (RQLQ). TOSS is calculated as the sum of the patients’ scoring of the 3 individual ocular symptoms (itching/burning, tearing/watering, and redness) on a 0 to 3 categorical severity scale (0 = absent, 1 = mild, 2 = moderate, 3 = severe) as reflective (rTOSS) or instantaneous scores (iTOSS). To assess efficacy, rTOSS and AM iTOSS were evaluated as described above for the TNSS. Patients’ perceptions of disease-specific quality of life were evaluated through use of the RQLQ, which assesses the impact of allergic rhinitis treatment through 28 items in 7 domains (activities, sleep, non-nose/eye symptoms, practical problems, nasal symptoms, eye symptoms, and emotional) on a 7-point scale where 0 = no impairment and 6 = maximum impairment. An overall RQLQ score is calculated from the mean of all items in the instrument. An absolute difference of ≥0.5 in mean change from baseline over placebo is considered the minimally important difference (MID) for the RQLQ.

Dose-Ranging Trial

The dose-ranging trial was a 2-week trial that evaluated the efficacy of 4 dosages of fluticasone furoate nasal spray (440, 220, 110, and 55 mcg) in patients with seasonal allergic rhinitis. In this trial, each of the 4 dosages of fluticasone furoate nasal spray demonstrated greater decreases in the rTNSS than placebo, and the difference was statistically significant (Table 3).

Table 3. Mean Change From Baseline in Reflective Total Nasal Symptom Score Over 2 Weeks in Patients With Seasonal Allergic Rhinitis
Treatment | n | Baseline; (AM; + PM) | Change; From; Baseline | Difference From Placebo
Treatment | n | Baseline; (AM; + PM) | Change; From; Baseline | LS Mean | 95% CI | P Value
Fluticasone furoate 440 mcg | 130 | 9.6 | -4.02 | -2.19 | -2.75, -1.62 | <0.001
Fluticasone furoate 220 mcg | 129 | 9.5 | -3.19 | -1.36 | -1.93, -0.79 | <0.001
Fluticasone furoate 110 mcg | 127 | 9.5 | -3.84 | -2.01 | -2.58, -1.44 | <0.001
Fluticasone furoate 55 mcg | 125 | 9.6 | -3.50 | -1.68 | -2.25, -1.10 | <0.001
Placebo | 128 | 9.6 | -1.83

Each of the 4 dosages of fluticasone furoate nasal spray also demonstrated greater decreases in the AM iTNSS than placebo, and the difference between each of the 4 fluticasone furoate treatment groups and placebo was statistically significant, indicating that the effect was maintained over the 24-hour dosing interval.

Seasonal Allergic Rhinitis Trials

Three clinical trials were designed to evaluate the efficacy of VERAMYST Nasal Spray 110 mcg once daily compared with placebo in patients with seasonal allergic rhinitis over a 2-week treatment period. In all 3 trials, VERAMYST Nasal Spray 110 mcg demonstrated a greater decrease from baseline in the rTNSS and AM iTNSS than placebo, and the difference from placebo was statistically significant. In terms of ocular symptoms, in all 3 seasonal allergic rhinitis trials, VERAMYST Nasal Spray 110 mcg demonstrated a greater decrease from baseline in the rTOSS than placebo and the difference from placebo was statistically significant. For the RQLQ in all 3 seasonal allergic rhinitis trials, VERAMYST Nasal Spray 110 mcg demonstrated greater decrease from baseline in the overall RQLQ than placebo, and the difference from placebo was statistically significant. The difference in the overall RQLQ score mean change from baseline between the groups treated with VERAMYST Nasal Spray and placebo ranged from -0.60 to -0.70 in the 3 trials, meeting the minimally important difference criterion. Table 4 displays the efficacy results from a representative trial in patients with seasonal allergic rhinitis.

Perennial Allergic Rhinitis Trials

One clinical trial was designed to evaluate the efficacy of VERAMYST Nasal Spray 110 mcg once daily compared with placebo in patients with perennial allergic rhinitis over a 4-week treatment period. VERAMYST Nasal Spray 110 mcg demonstrated a greater decrease from baseline in the rTNSS and AM iTNSS than placebo, and the difference from placebo was statistically significant. Similar to patients with seasonal allergic rhinitis, the improvement of nasal symptoms with VERAMYST Nasal Spray in patients with perennial allergic rhinitis persisted for a full 24 hours, as evaluated by AM iTNSS immediately prior to the next dose. However, unlike the trials in patients with seasonal allergic rhinitis, patients with perennial allergic rhinitis who were treated with VERAMYST Nasal Spray 110 mcg did not demonstrate statistically significant improvement from baseline in rTOSS or in disease-specific quality of life as measured by the RQLQ compared with placebo. In addition, the overall RQLQ score mean change from baseline difference between the group treated with VERAMYST Nasal Spray and the placebo group was -0.23, which did not meet the minimally important difference of ≥0.5. Table 4 displays the efficacy results from the clinical trial in patients with perennial allergic rhinitis.

Table 4. Mean Changes in Efficacy Variables in Adult and Adolescent Patients With Seasonal or Perennial Allergic Rhinitis
Treatment | n | Baseline | Change From; Baseline –; LS Mean | Difference From Placebo
Treatment | n | Baseline | Change From; Baseline –; LS Mean | LS Mean |  |  | 95% CI | P Value
Reflective Total Nasal Symptom Scores
Seasonal allergic rhinitis trial
Fluticasone furoate 110 mcg | 151 | 9.6 | -3.55 |  | -1.47 | -2.01, -0.94 |  | <0.001
Placebo | 147 | 9.9 | -2.07
Perennial allergic rhinitis trial
Fluticasone furoate 110 mcg | 149 | 8.6 | -2.78 |  | -0.71 | -1.20, -0.21 |  | 0.005
Placebo | 153 | 8.7 | -2.08
Instantaneous Total Nasal Symptom Scores
Seasonal allergic rhinitis trial
Fluticasone furoate 110 mcg | 151 | 9.4 | -2.90 |  | -1.38 | -1.90, -0.85 |  | <0.001
Placebo | 147 | 9.3 | -1.53
Perennial allergic rhinitis trial
Fluticasone furoate 110 mcg | 149 | 8.2 | -2.45 |  | -0.71 | -1.20, -0.21 |  | 0.006
Placebo | 153 | 8.3 | -1.75
Reflective Total Ocular Symptom Scores
Seasonal allergic rhinitis trial
Fluticasone furoate 110 mcg | 151 | 6.6 | -2.23 |  | -0.60 | -1.01, -0.19 |  | 0.004
Placebo | 147 | 6.5 | -1.63
Perennial allergic rhinitis trial
Fluticasone furoate 110 mcg | 149 | 4.8 | -1.39 |  | -0.15 | -0.52, 0.22 |  | 0.428
Placebo | 153 | 5.0 | -1.24
Rhinoconjunctivitis Quality of Life Questionnaire
Seasonal allergic rhinitis trial
Fluticasone furoate 110 mcg | 144 | 3.9 | -1.77 |  | -0.60 | -0.93, -0.28 |  | <0.001
Placebo | 144 | 3.9 | -1.16
Perennial allergic rhinitis trial
Fluticasone furoate 110 mcg | 143 | 3.5 | -1.41 |  | -0.23 | -0.59, 0.13 |  | 0.214
Placebo | 151 | 3.4 | -1.18

Onset of action was evaluated by frequent instantaneous TNSS assessments after the first dose in the clinical trials in patients with seasonal allergic rhinitis and perennial allergic rhinitis. Onset of action was generally observed within 24 hours in patients with seasonal allergic rhinitis. In patients with perennial rhinitis, onset of action was observed after 4 days of treatment. Continued improvement in symptoms was observed over approximately 1 and 3 weeks in patients with seasonal or perennial allergic rhinitis, respectively.

Pediatric Patients Aged 2 to 11 Years

The efficacy and safety of VERAMYST Nasal Spray were evaluated in 1,112 children (633 boys and 479 girls), mean age of 8 years with seasonal or perennial allergic rhinitis in 2 controlled clinical trials. The pediatric patients were treated with VERAMYST Nasal Spray 55 or 110 mcg once daily for 2 to 12 weeks (n = 369 for each dose). The trials were similar in design to the trials conducted in adolescents and adults; however, the efficacy determination was made from patient- or parent/guardian-reported TNSS for children aged 6 to <12 years. Children treated with VERAMYST Nasal Spray generally exhibited greater decreases in nasal symptoms than placebo-treated patients. In seasonal allergic rhinitis, the difference in rTNSS was statistically significant only for the 110-mcg dose. In perennial allergic rhinitis, the difference in rTNSS was statistically significant only for the 55-mcg dose. Changes in rTOSS in the seasonal allergic rhinitis trial were not statistically significant compared with placebo for either dose. rTOSS was not assessed in the perennial allergic rhinitis trial. Table 5 displays the efficacy results from the clinical trials in patients with perennial allergic rhinitis and seasonal allergic rhinitis in children aged 6 to <12 years. Efficacy in children aged 2 to <6 years was supported by a numerical decrease in the rTNSS.

Table 5. Mean Changes in Efficacy Variables in Pediatric Patients Aged 6 to <12 Years With Seasonal or Perennial Allergic Rhinitis
Treatment | n | Baseline | Change From Baseline – LS Mean | Difference From Placebo
Treatment | n | Baseline | Change From Baseline – LS Mean | LS Mean |  |  | 95% CI | P Value
Reflective Total Nasal Symptom Scores
Seasonal allergic rhinitis trial
Fluticasone furoate 55 mcg | 151 | 8.6 | -2.71 |  | -0.16 | -0.69, 0.37 |  | 0.553
Fluticasone furoate 110 mcg | 146 | 8.5 | -3.16 |  | -0.62 | -1.15, -0.08 |  | 0.025
Placebo | 149 | 8.4 | -2.54
Perennial allergic rhinitis trial
Fluticasone furoate 55 mcg | 144 | 8.5 | -4.16 |  | -0.75 | -1.24, -0.27 |  | 0.003
Fluticasone furoate 110 mcg | 140 | 8.6 | -3.86 |  | -0.45 | -0.95, 0.04 |  | 0.073
Placebo | 147 | 8.5 | -3.41
Instantaneous Total Nasal Symptom Scores
Seasonal allergic rhinitis trial
Fluticasone furoate 55 mcg | 151 | 8.4 | -2.37 |  | -0.23 | -0.77, 0.30 |  | 0.389
Fluticasone furoate 110 mcg | 146 | 8.3 | -2.80 |  | -0.67 | -1.21, -0.13 |  | 0.015
Placebo | 149 | 8.4 | -2.13
Perennial allergic rhinitis trial
Fluticasone furoate 55 mcg | 144 | 8.3 | -3.62 |  | -0.75 | -1.24, -0.27 |  | 0.002
Fluticasone furoate 110 mcg | 140 | 8.3 | -3.52 |  | -0.65 | -1.14, -0.16 |  | 0.009
Placebo | 147 | 8.3 | -2.87
Reflective Total Ocular Symptom Scores
Seasonal allergic rhinitis trial
Fluticasone furoate 55 mcg | 151 | 4.4 | -1.26 |  | 0.04 | -0.33, 0.41 |  | 0.826
Fluticasone furoate 110 mcg | 146 | 4.1 | -1.45 |  | -0.15 | -0.52, 0.22 |  | 0.426
Placebo | 149 | 3.8 | -1.30

16 HOW SUPPLIED/STORAGE AND HANDLING

VERAMYST Nasal Spray, 27.5 mcg per spray, is supplied in a brown glass bottle enclosed in a nasal device with a nozzle and a mist-release button to actuate the spray in a box of 1 (NDC 54868-6168-0) with FDA-Approved Patient Labeling (see Patient Instructions for Use for proper actuation of the device).

Each bottle contains a net fill weight of 10 g of white, liquid suspension and will provide 120 metered sprays. After priming [see Dosage and Administration (2)], each spray delivers a fine mist containing 27.5 mcg of fluticasone furoate in 50 microliters of formulation through the nozzle. The contents of the bottle can be viewed through an indicator window. Shake the contents well before each use. The correct amount of medication in each spray cannot be assured before the initial priming and after 120 sprays have been used, even though the bottle is not completely empty. The nasal device should be discarded after 120 sprays have been used.

Store the device in the upright position with the cap in place between 15° and 30°C (59° and 86°F). Do not freeze or refrigerate.

17 PATIENT COUNSELING INFORMATION

See FDA-Approved Patient Labeling.

17.1 Local Nasal Effects

Patients should be informed that treatment with VERAMYST Nasal Spray may lead to adverse reactions, which include epistaxis and nasal ulceration. Candida infection may also occur with treatment with VERAMYST Nasal Spray. In addition, nasal corticosteroids are associated with nasal septal perforation and impaired wound healing. Patients who have experienced recent nasal ulcers, nasal surgery, or nasal trauma should not use VERAMYST Nasal Spray until healing has occurred [see Warnings and Precautions (5.1)].

17.2 Cataracts and Glaucoma

Patients should be informed that glaucoma and cataracts are associated with nasal and inhaled corticosteroid use. Patients should inform his/her health care provider if a change in vision is noted while using VERAMYST Nasal Spray [see Warnings and Precautions (5.2)].

17.3 Hypersensitivity Reactions, Including Anaphylaxis

Patients should be aware that hypersensitivity reactions, including anaphylaxis, angioedema, rash, and urticaria, may occur after administration of VERAMYST Nasal Spray. If such reactions occur, patients should discontinue use of VERAMYST Nasal Spray [see Warnings and Precautions (5.3)].

17.4 Immunosuppression

Patients who are on immunosuppressant doses of corticosteroids should be warned to avoid exposure to chickenpox or measles and, if exposed, to consult their physician without delay. Patients should be informed of potential worsening of existing tuberculosis, fungal, bacterial, viral or parasitic infections, or ocular herpes simplex [see Warnings and Precautions (5.4)].

17.5 Use Daily for Best Effect

Patients should use VERAMYST Nasal Spray on a regular once-daily basis for optimal effect. VERAMYST Nasal Spray, like other corticosteroids, does not have an immediate effect on rhinitis symptoms. Although significant improvement is usually achieved within 24 hours in patients with seasonal allergic rhinitis and 4 days in patients with perennial allergic rhinitis, maximum benefit may not be reached for several days. The patient should not increase the prescribed dosage but should contact the physician if symptoms do not improve or if the condition worsens.

17.6 Keep Spray Out of Eyes

Patients should be informed to avoid spraying VERAMYST Nasal Spray in their eyes.

17.7 Potential Drug Interactions

Patients should be advised that coadministration of VERAMYST Nasal Spray and ritonavir is not recommended and to be cautious if coadministrating with ketoconazole.

GlaxoSmithKline

Research Triangle Park, NC 27709

©2010, GlaxoSmithKline. All rights reserved.

March 2010

VRM:5PI

Relabeling of "Additional Barcode Label" by:
Physicians Total Care, Inc.
Tulsa, OK 74146

PATIENT INFORMATION

VERAMYST® [VAIR-uh-mist]

(fluticasone furoate)

Nasal Spray

FOR INTRANASAL USE ONLY

Read the Patient Information that comes with VERAMYST Nasal Spray carefully before you start using it and each time you get a refill. There may be new information. Keep the leaflet for reference because it gives you a summary of important information about VERAMYST Nasal Spray. This leaflet does not take the place of talking to your healthcare provider about your medical condition or your treatment.

What is VERAMYST Nasal Spray?

VERAMYST is a medicine that treats seasonal and year-round allergy symptoms in adults and children 2 years old and older.

VERAMYST contains fluticasone furoate, which is a man-made (synthetic) corticosteroid. Corticosteroids are natural substances found in the body that reduce inflammation. When you spray VERAMYST into your nose, it helps reduce the nasal symptoms of allergic rhinitis (inflammation of the lining of the nose), such as stuffy nose, runny nose, itching, and sneezing. VERAMYST may also help red, itchy, and watery eyes in adults and teenagers with seasonal allergic rhinitis.

Your healthcare provider has prescribed VERAMYST to treat your symptoms of allergic rhinitis.

What should I tell my healthcare provider before taking VERAMYST Nasal Spray?

Tell your healthcare provider about all of your medical conditions, including if you are:

- pregnant (or planning to become pregnant).
- breastfeeding a baby.
- allergic to any of the ingredients in VERAMYST or any other nasal corticosteroid. See “What are the ingredients in VERAMYST Nasal Spray?” below for a complete list of ingredients.
- exposed to chickenpox or measles.
- feeling unwell or have any symptoms that you do not understand.

Tell your healthcare provider about all the medicines you take, including prescription and non-prescription medicines, vitamins, and herbal products. VERAMYST and other medicines may affect each other, causing side effects. Be certain to tell your healthcare provider if you are taking a medicine that contains ritonavir (commonly used to treat HIV infection or AIDS).

How should I use VERAMYST Nasal Spray?

- This medicine is for use in the nose only. Do not spray it in your eyes or mouth.
- An adult should help a young child use this medicine.
- This medicine has been prescribed for you by your healthcare provider. DO NOT give this medicine to anyone else.
- Use VERAMYST exactly as your healthcare provider tells you to. DO NOT take more of your medicine or take it more often than your healthcare provider tells you. The prescription label will usually tell you how many sprays to take and how often. If it does not or if you are not sure, ask your healthcare provider or pharmacist.
- For people aged 12 years and older, the usual starting dosage is 2 sprays in each nostril, once a day. After you begin to feel better, your healthcare provider may tell you that 1 spray in each nostril once a day may be enough for you.
- For children aged 2 to 11 years, the usual starting dosage is 1 spray in each nostril, once a day. Your healthcare provider may tell you to take 2 sprays in each nostril once a day. After you begin to feel better, your healthcare provider may change the dosage to 1 spray in each nostril once a day. An adult should help a young child use this medicine.
- Do not use VERAMYST after 120 sprays (plus the initial priming sprays) have been used or after the expiration date, whichever comes first. (The sample bottle contains 30 sprays.) The bottle may not be completely empty. The expiration date is printed as “EXP” on the product label and box. Before you throw away VERAMYST, talk to your healthcare provider to see if you need a refill of your prescription. If your healthcare provider tells you to continue using VERAMYST, throw away the empty or expired bottle and use a new bottle of VERAMYST. Follow the Patient Instructions for Use below.
- Do not take extra doses or stop taking VERAMYST without telling your healthcare provider.
- VERAMYST may begin to work within 24 hours after you take your first dose. It may take several days before it has its greatest effect.
- You will get the best results if you keep using VERAMYST regularly each day without missing a dose. If you miss a dose by several hours, just take your next dose at the usual time. DO NOT take an extra dose.

What are the possible side effects of VERAMYST Nasal Spray?

Some patients taking VERAMYST had nosebleeds or nasal sores. These are not all of the possible side effects of VERAMYST. For more information, ask your healthcare provider or pharmacist.

What are other risks of using VERAMYST?

- Some patients may get a nasal fungal infection. This happened in about 1 out of 1,000 patients in clinical studies with VERAMYST.
- Corticosteroids can slow the healing of wounds. Do not use VERAMYST until your nose has healed if you have a sore in your nose, if you have surgery on your nose, or if your nose has been injured.
- Some patients may have eye problems, including glaucoma and cataracts. You should have regular eye exams.
- Immune system effects may increase the risk of infections.
- Corticosteroids may slow growth in children. A child taking VERAMYST should have his/her growth checked regularly.

What should I know about allergic rhinitis?

“Rhinitis” means inflammation of the lining of the nose. It is sometimes called “hay fever.” Allergic rhinitis can be caused by allergies to pollen, animal dander, house dust mite, and mold spores. If you have allergic rhinitis, your nose becomes stuffy, runny, and itchy. You may also sneeze a lot. You may also have red, itchy, watery eyes; itchy throat; or blocked, itchy ears.

What are the ingredients in VERAMYST Nasal Spray?

Active ingredient: fluticasone furoate.

Inactive ingredients: 0.015% w/w benzalkonium chloride, dextrose anhydrous, edetate disodium, microcrystalline cellulose, carboxymethylcellulose sodium, polysorbate 80, and purified water.

Patient Instructions for Use

Read this leaflet carefully before you start to use VERAMYST Nasal Spray. If you have any questions, ask your healthcare provider or pharmacist.

The parts of the VERAMYST Nasal Spray

VERAMYST Nasal Spray comes in a brown glass bottle inside a nasal device. It contains 120 sprays (or 30 sprays if it is a sample) plus the first priming sprays. Be careful not to drop it. If you accidentally drop the device, check it for damage. If the device is damaged, return it to your pharmacist.

The Cap has a tab that keeps the Mist-Release Button from being pressed accidentally. It also helps keep the nozzle clean. Do not throw the cap away. Always keep the cap on the device when you are not using it.

The Nozzle is small and short, so it will fit inside your nose. The medicine comes out of the nozzle.

Pressing the Mist-Release Button sprays a measured amount of medicine from the nozzle as a gentle, fine mist. Because the button is on the side of the device, you can keep the nozzle in the right place in your nose while you press the button.

The Window lets you see if there is medicine left in the bottle when you hold it in front of a bright light. (You may not be able to see the medicine in a full bottle because the liquid level is above the window.)

How to prime your VERAMYST Nasal Spray

Priming helps to make sure you always get the same full dose of medicine. You need to prime VERAMYST Nasal Spray:

- before you use a new bottle for the first time.
- if you have not used your VERAMYST Nasal Spray for 30 days or longer.
- if the cap has been left off the bottle for 5 days or longer.
- if the device does not seem to be working right.

To prime VERAMYST Nasal Spray:

Figure 1
Figure 2
Figure 3

1. With the cap on, shake the device well (Figure 1). This is important to make the medicine a liquid that will spray.
2. Take the cap off by squeezing the finger grips and pulling it straight off (Figure 2).
3. Hold the device with the nozzle pointing up and away from you. Place your thumb or fingers on the button. Press the button all the way in 6 times or until a fine mist sprays from the nozzle (Figure 3). Your VERAMYST Nasal Spray is now ready to use.

How to use your VERAMYST Nasal Spray

Follow the instructions below. If you have any questions, ask your healthcare provider or pharmacist.

Before taking a dose of VERAMYST Nasal Spray, gently blow your nose to clear your nostrils. Shake the bottle well. Then do these 3 simple steps: Place, Press, Repeat.

Figure 4
Figure 5
Figure 6
Figure 7

1. PLACE

Tilt your head forward a little bit. Hold the device upright. PLACE the nozzle in one of your nostrils (Figure 4).

Point the end of the nozzle toward the side of your nose, away from the center of your nose (septum). This helps get the medicine to the right part of your nose.

2. PRESS

PRESS the button all the way in 1 time to spray the medicine in your nose while you are breathing in (Figure 5).

Do not get any spray in your eyes. If you do, rinse your eyes well with water.

Take the nozzle out of your nose. Breathe out through your mouth (Figure 6).

3. REPEAT

To deliver the medicine to the other nostril, REPEAT Steps 1 and 2 in the other nostril (Figure 7).

If your healthcare provider has told you to take 2 sprays in each nostril, do Steps 1-3 again.

Put the cap back on the device after you have finished taking your dose.

How to clean your VERAMYST Nasal Spray

After each use: wipe the nozzle with a clean, dry tissue (Figure 8). Never try to clean the nozzle with a pin or anything sharp because this will damage the nozzle. Do not use water to clean the nozzle.

Figure 8

Once a week: clean the inside of the cap with a clean, dry tissue (Figure 9). This will help keep the nozzle from getting blocked.

Figure 9

How to store your VERAMYST Nasal Spray

- Keep your VERAMYST Nasal Spray and all medicines out of the reach of children.
- Store between 59° and 86°F (15° and 30°C). Do not refrigerate or freeze.
- Store with the cap on.
- Store in an upright position.

GlaxoSmithKline

Five Moore Drive

Research Triangle Park, NC 27709

©2009, GlaxoSmithKline. All rights reserved.

September 2009 VRM:6PIL

PACKAGE LABEL

Principal Display Panel

Veramyst®

(fluticasone furoate)

Nasal Spray

27.5 mcg per spray

For Intranasal Use Only.

ATTENTION PHARMACIST: Dispense with enclosed Patient Information leaflet.

Important: Read accompanying directions carefully.

Rx only

120 Metered Sprays

10 g net fill weight

Before Use: VERAMYST Nasal Spray should be primed before using for the first time by releasing 6 test sprays into the air away from the face. In cases where it has not been used for more than 30 days or if the cap has been left off the bottle for 5 days or longer, prime the pump again until a fine mist appears.

Shake well before each use.

Store between 15o and 30oC (59o and 86oF). Do not refrigerate or freeze.

Store with the cap in an upright position.

Keep out of the reach of children.

For information on Veramyst Nasal Spray, call 1-877-665-6673 or go to www.Veramyst.com.